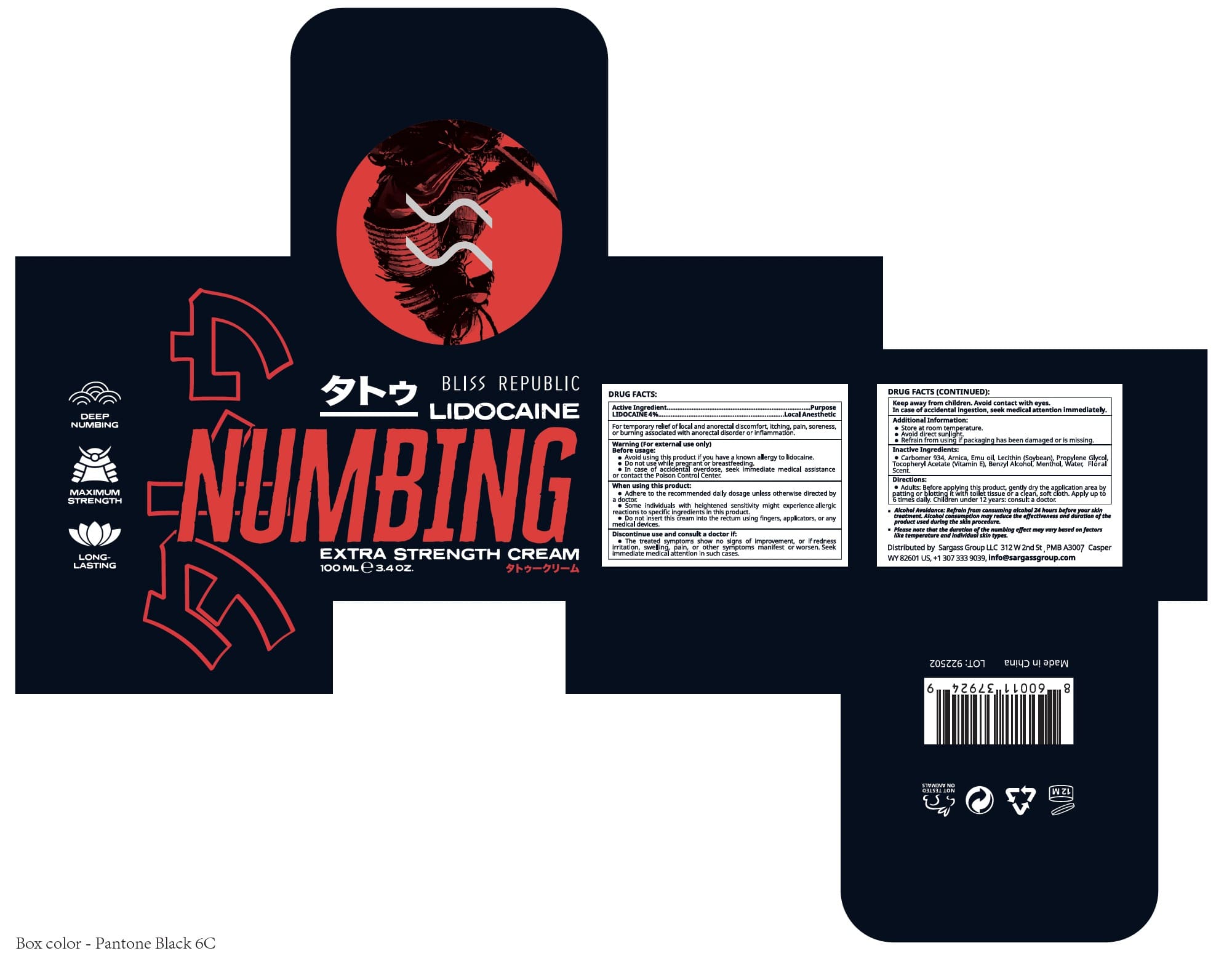 DRUG LABEL: Bliss Republic
NDC: 84028-124 | Form: CREAM
Manufacturer: Sargass Group Limited Liability Company
Category: otc | Type: HUMAN OTC DRUG LABEL
Date: 20250521

ACTIVE INGREDIENTS: LIDOCAINE HYDROCHLORIDE 4 mg/100 mL
INACTIVE INGREDIENTS: WATER; LECITHIN, SOYBEAN; MENTHOL; CARBOMER 934; ALPHA-TOCOPHEROL ACETATE; ARNICA MONTANA FLOWER; PROPYLENE GLYCOL; BENZYL ALCOHOL

BLISS REPUBLIC LIDOCAINE NUMBING CREAM

Active Ingredient(s)

LIDOCAINE 4%_ _ _ _ _ _ _ _ _ _ _ _ _ _ _ _ _ _ _ _ _ _ Local Anesthetic

Purpose

Topical Anesthetic

Use

For temporary relief of local and anorectal discomfort, itching, pain, soreness, or burning associated with anorectal disorder or inflammation.

Warnings

(For external use only)

Before usage:

Avoid using this product if you have a known allergy to lidocaine.
Do not use while pregnant or breastfeeding.

In case of accidental overdose, seek immediate medical assistance or contact the Poison Control Center.

When using this product:

Adhere to the recommended daily dosage unless otherwise directed by a doctor.
Some individuals with heightened sensitivity might experience allergic reactions to specific ingredients in this product.

Do not insert this cream into the rectum using fingers, applicators, or any medical devices.

KEEP OUT OF REACH OF CHILDREN

Keep away from children. Avoid contact with eyes. In case of accidental ingestion, seek medical attention immefiately.

Discontinue use and consult a doctor if:

The treated symptoms show no signs of improvement, or if redness, irritation, swelling, pain, or other symptoms manifest or worsen. Seek immediate medical attention in such cases.

Directions

Adults: Before applying this product, gently dry the application area by patting or blotting it with toilet tissue or a clean, soft cloth.

Apply up to 6 times daily. Children under 12 years: consult a doctor.

Other information

Additional Information:

Store at room temperature. Avoid direct sunlight. Refrain from using if packaging has been damaged or is missing.

Inactive ingredients

Carbomer 934, Arnica, Emu oil, Lecithin (Soybean), Propylene Glycol, Tocopheryl Acetate (Vitamin E), Benzyl Alcohol, Menthol, Water Floral scent